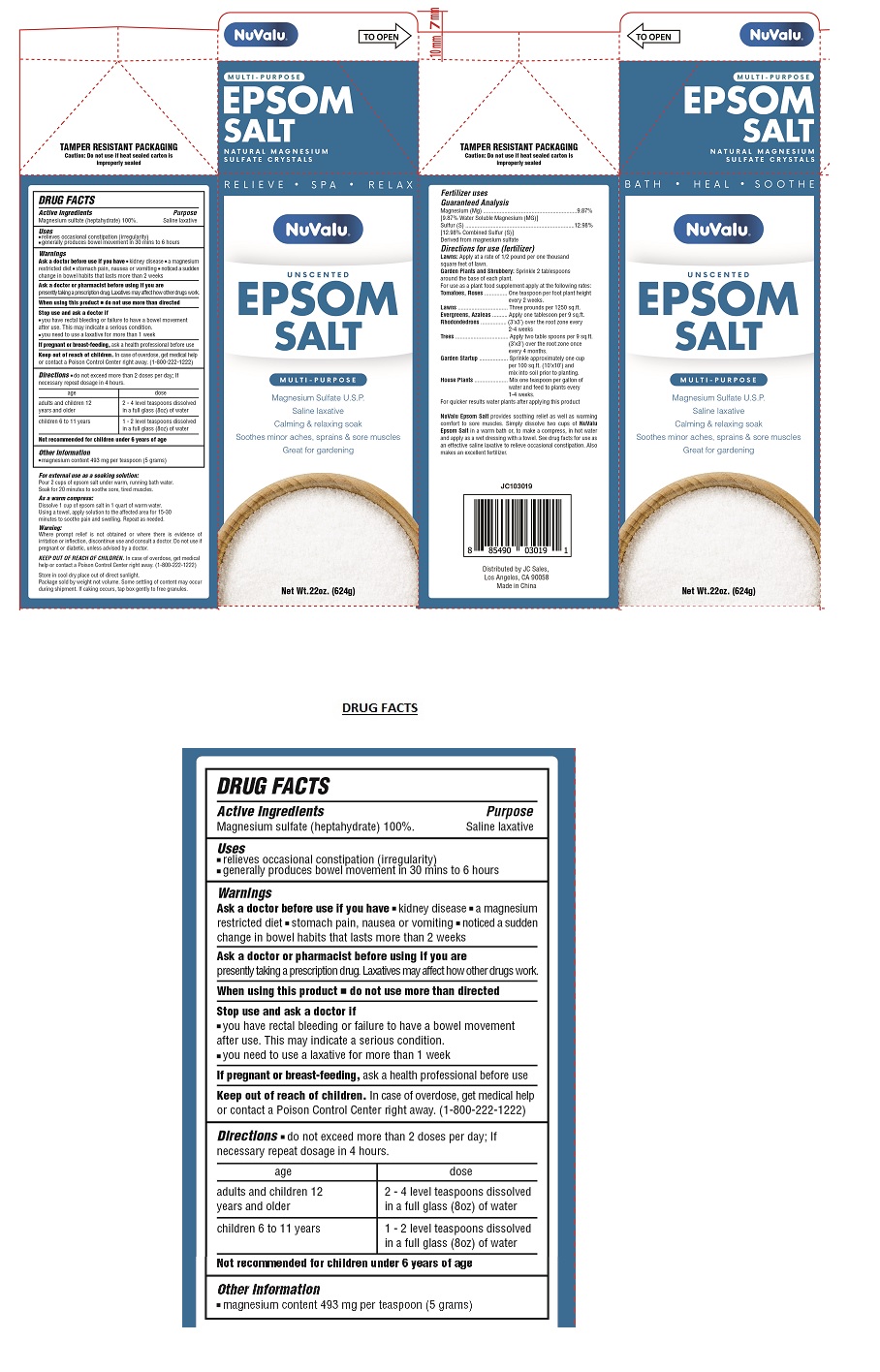 DRUG LABEL: NuValu Epsom Salt
NDC: 72520-001 | Form: GRANULE
Manufacturer: J C SALES
Category: otc | Type: HUMAN OTC DRUG LABEL
Date: 20241204

ACTIVE INGREDIENTS: MAGNESIUM SULFATE HEPTAHYDRATE 100 g/100 g

NuValu Epsom Salt

Active Ingredients

Magnesium sulfate (heptahydrate) 100%

Purpose

Saline laxative

Uses

- relieves occasional constipation (irregularity)
- generally produces bowel movement in 30 mins to 6 hours

Warnings

Ask a doctor before use if you have • kidney disease • a magnesium restricted diet • stomach pain, nausea or vomiting • noticed a sudden change in bowel habits that lasts more than 2 weeks

Ask a doctor or pharmacist before using if you are

presently taking a prescription drug. Laxatives may affect how other drugs work.

When using this product • do not use more than directed

Stop use and ask a doctor if

- you have rectal bleeding or failure to have a bowel movement after use. This may indicate a serious condition.
- you need to use a laxative for more than 1 week

If pregnant or breast-feeding, ask a health professional before use

Keep out of reach of children. In case of overdose, get medical help or contact a Poison Control Center right away. (1-800-222-1222)

Directions

• do not exceed more than 2 doses per day; If necessary repeat dosage in 4 hours.

age | dose
adults and children 12 years and older | 2-4 level teaspoons dissolved in a full glass (8oz) of water
children 6 to 11 years | 1-2 level teaspoons dissolved in a full glass (8oz) of water

Not recommended for children under 6 years of age.

Other Information

- magnesium content 493 mg per teaspoon (5 grams)

Store in cool dry place out of direct sunlight.

Inactive Ingredients

none

UNSCENTED

MULTI-PURPOSE

Magnesium sulfate U.S.P

Saline laxative

TAMPER RESISTANT PACKAGING

Caution: Do not use if heat sealed carton is improperly sealed

Package sold by weight not volume. Some settling of content may occur during shipment. If caking occurs, tap pouch gently to free granules.

Distributed by JC Sales,

Los Angeles, CA 90058

Made in China